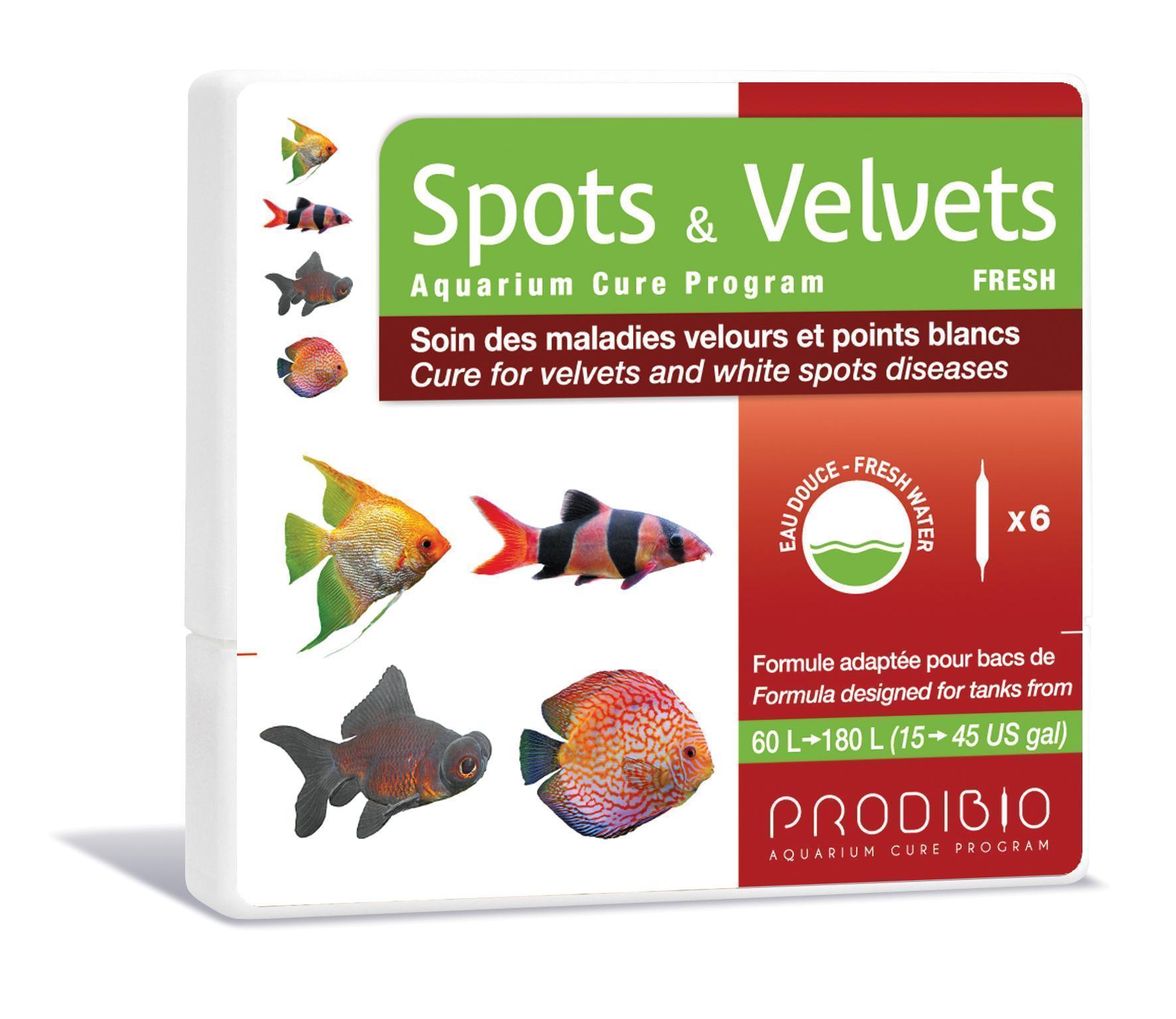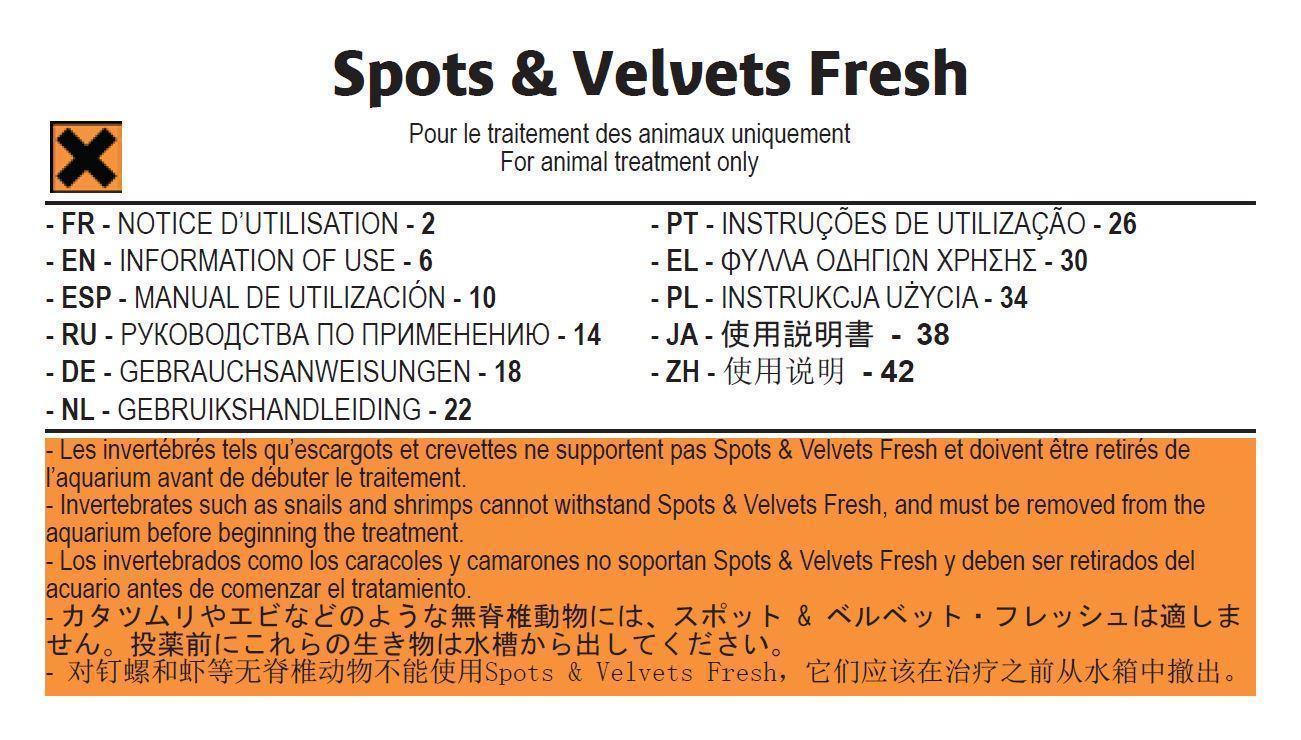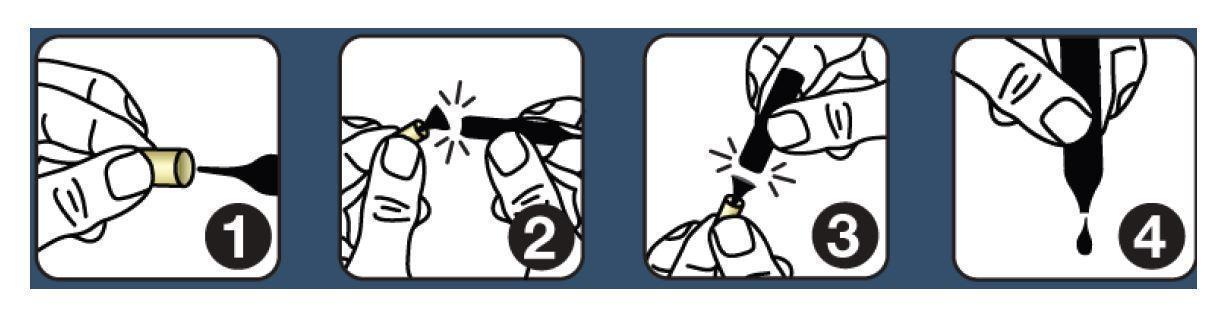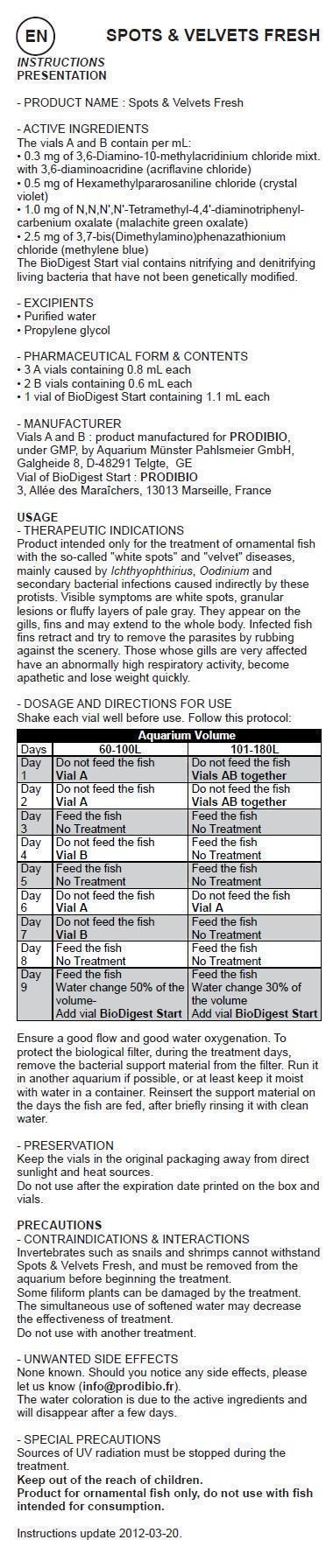 DRUG LABEL: SPOTS and VELVETS Aquarium Cure Program FRESH
NDC: 86048-004 | Form: KIT | Route: ORAL
Manufacturer: Prodibio SAS
Category: animal | Type: OTC ANIMAL DRUG LABEL
Date: 20150903

ACTIVE INGREDIENTS: GENTIAN VIOLET 0.5 mg/1 mL; MALACHITE GREEN OXALATE 1.0 mg/1 mL; ACRIFLAVINE HYDROCHLORIDE 0.3 mg/1 mL; METHYLENE BLUE 2.5 mg/1 mL; ACRIFLAVINE HYDROCHLORIDE 0.3 mg/1 mL; GENTIAN VIOLET 0.5 mg/1 mL; MALACHITE GREEN OXALATE 1.0 mg/1 mL; METHYLENE BLUE 2.5 mg/1 mL
INACTIVE INGREDIENTS: WATER; PROPYLENE GLYCOL; WATER; PROPYLENE GLYCOL

SPOTS & VELVETS Aquarium Cure Program FRESH

- PRODUCT NAME : Spots & Velvets Fresh

- ACTIVE INGREDIENTS

The vials A and B contain per mL:
• 0.3 mg of 3,6-Diamino-10-methylacridinium chloride mixt. with 3,6-diaminoacridine (acriflavine chloride)
• 0.5 mg of Hexamethylpararosaniline chloride (crystal violet)
• 1.0 mg of N,N,N',N'-Tetramethyl-4,4'-diaminotriphenylcarbenium oxalate (malachite green oxalate)
• 2.5 mg of 3,7-bis(Dimethylamino)phenazathionium chloride (methylene blue)
The BioDigest Start vial contains nitrifying and denitrifying living bacteria that have not been genetically modified.

- EXCIPIENTS

• Purified water
• Propylene glycol

- PHARMACEUTICAL FORM & CONTENTS

• 3 A vials containing 0.8 mL each
• 2 B vials containing 0.6 mL each
• 1 vial of BioDigest Start containing 1.1 mL each

- MANUFACTURER

Vials A and B : product manufactured for PRODIBIO,
under GMP, by Aquarium Münster Pahlsmeier GmbH,
Galgheide 8, D-48291 Telgte, GE
Vial of BioDigest Start : PRODIBIO
3, Allée des Maraîchers, 13013 Marseille, France

USAGE

- THERAPEUTIC INDICATIONS
Product intended only for the treatment of ornamental fish with the so-called "white spots" and "velvet" diseases, mainly caused by Ichthyophthirius, Oodinium and secondary bacterial infections caused indirectly by these protists. Visible symptoms are white spots, granular lesions or fluffy layers of pale gray. They appear on the gills, fins and may extend to the whole body. Infected fish fins retract and try to remove the parasites by rubbing against the scenery. Those whose gills are very affected have an abnormally high respiratory activity, become apathetic and lose weight quickly.

- DOSAGE AND DIRECTIONS FOR USE

Shake each vial well before use. Follow this protocol:

Aquarium Volume
Days | 60-100L | 101-180L
Day 1 | Do not feed the fish Vial A | Do not feed the fish Vials AB together
Day 2 | Do not feed the fish; Vial A | Do not feed the fish Vials AB together
Day 3 | Feed the fish No Treatment | Feed the fish No Treatment
Day 4 | Do not feed the fish Vial B | Feed the fish No Treatment
Day 5 | Feed the fish No Treatment | Feed the fish No Treatment
Day 6 | Do not feed the fish; Vial A | Do not feed the fish; Vial A
Day 7 | Do not feed the fish Vial B | Feed the fish No Treatment
Day 8 | Feed the fish No Treatment | Feed the fish No Treatment
Day 9 | Feed the fish; Water change 50% of the volume- Add the vial BioDigest Start | Feed the fish Water change 30% of the volume Add vial BioDigest Start

Ensure a good flow and good water oxygenation. To protect the biological filter, during the treatment days, remove the bacterial support material from the filter. Run it in another aquarium if possible, or at least keep it moist with water in a container. Reinsert the support material on the days the fish are fed, after briefly rinsing it with clean water.

- PRESERVATION

Keep the vials in the original packaging away from direct sunlight and heat sources.
Do not use after the expiration date printed on the box and vials.

PRECAUTIONS - CONTRAINDICATIONS & INTERACTIONS

Invertebrates such as snails and shrimps cannot withstand Spots & Velvets Fresh, and must be removed from the aquarium before beginning the treatment.
Some filiform plants can be damaged by the treatment.
The simultaneous use of softened water may decrease the effectiveness of treatment.
Do not use with another treatment.

- UNWANTED SIDE EFFECTS

None known. Should you notice any side effects, please let us know (info@prodibio.fr).
The water coloration is due to the active ingredients and will disappear after a few days.

- SPECIAL PRECAUTIONS

Sources of UV radiation and skimmers must be stopped during the treatment.
Product for ornamental fish only, do not use with fish intended for consumption.

Instructions update 2012-08.
This veterinary medicines is marketed in accordinance with the Small Animal Exception Scheme

- Special precautions for the disposal of unused pharmaceuticals

Dispose od drugs not entirely used up at the respective collecting points

Disposal advice: after use, vials must be thrown in recyclable glass rubbish